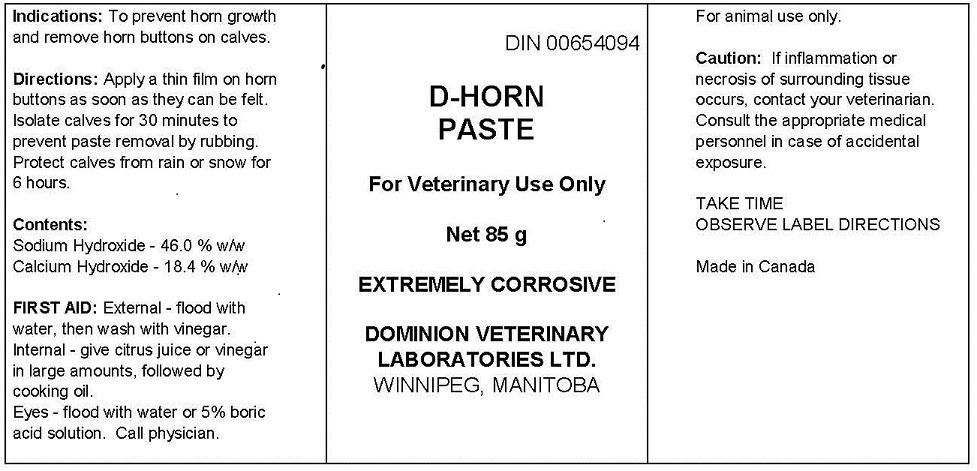 DRUG LABEL: D-HORN
NDC: 64120-101 | Form: PASTE
Manufacturer: DOMINION VETERINARY LABORATORIES LTD.
Category: animal | Type: OTC ANIMAL DRUG LABEL
Date: 20211111

ACTIVE INGREDIENTS: SODIUM HYDROXIDE 46.0 g/100 mL; CALCIUM HYDROXIDE 18.4 g/100 mL

DOMINION VETERINARY LABORATORIES - D-HORN PASTE

ACTIVE INGREDIENTS

SODIUM HYDROXIDE 46.0%

CALCIUM HYDROXIDE 18.4%

INDICATIONS

TO PREVENT HORN GROWTH AND REMOVE HORN BUTTONS ON CALVES.

WARNINGS

FOR ANIMAL USE ONLY

CAUTIONS: IF INFLAMMATION OR NECROSIS OF SURROUNDING TISSUE OCCURS, CONTACT YOUR VETERINARIAN. CONSULT THE APPROPRIATE MEDICAL PERSONNEL IN CASE OF ACCIDENTAL EXPOSURE.

TAKE TIME

OBSERVE LABEL DIRECTIONS

DIRECTIONS

APPLY A THIN FILM ON HORN BUTTONS AS SOON AS THEY CAN BE FELT.

ISOLATE CALVES FOR 30 MINUTES TO PREVENT PASTE REMOVAL BY RUBBING.

PORTECT CALVES FROM RAIN OR SNOW FOR 6 HOURS.

FIRST AID

EXTERNAL: FLOOD WITH WATER, THEN WASH WITH VINEGAR.

INTERNAL: GIVE CITRUS JUICE OR VINEGAR IN LARGE AMOUNTS, FOLLWED BY COOKING OIL.

EYES: FLOOD WITH WATER OR 5% BORIC ACID SOLUTION. CALL PHYSICIAN.